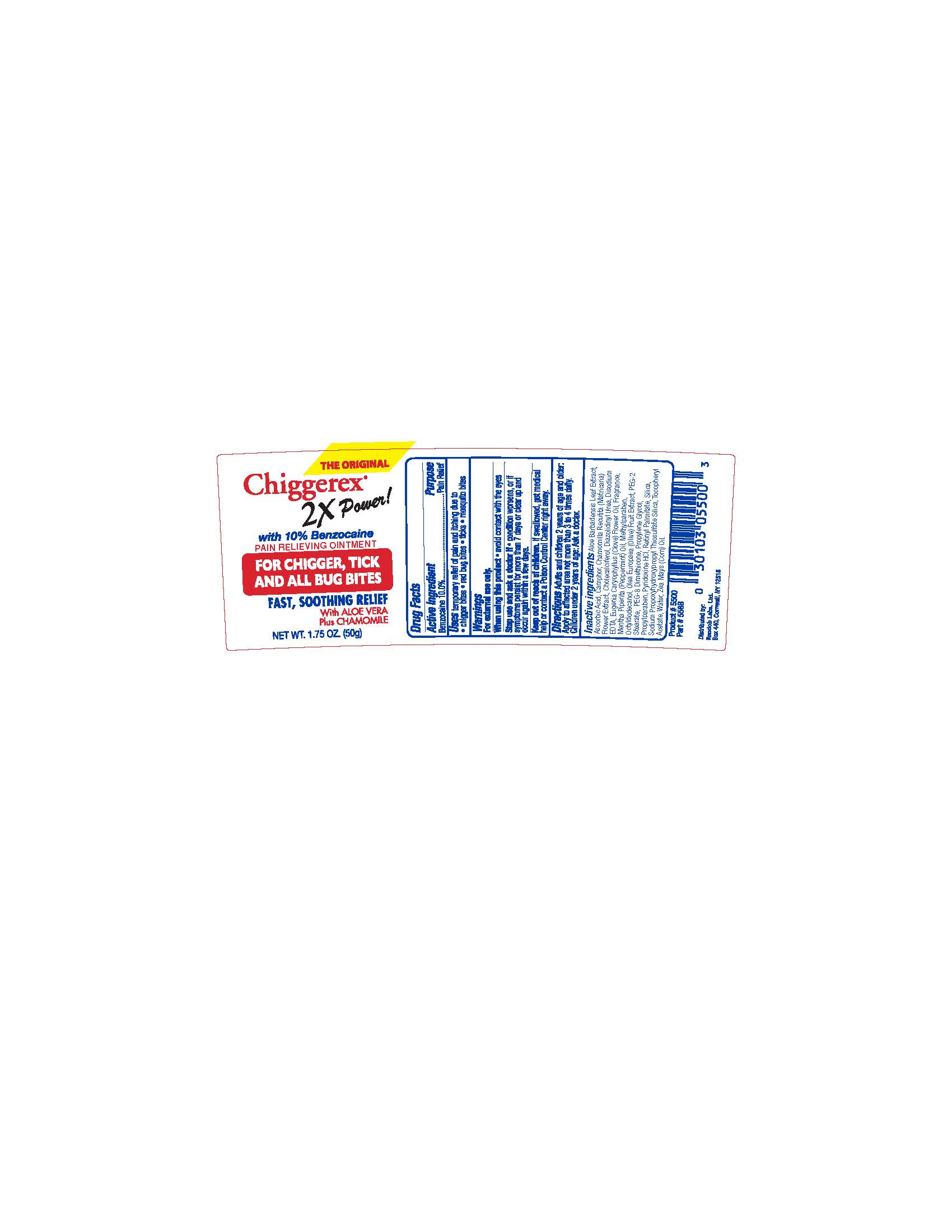 DRUG LABEL: Chiggerex
NDC: 52412-350 | Form: CREAM
Manufacturer: RANDOB LABS, LTD. DBA CROSSINGWELL CONSUMER HEALTH
Category: otc | Type: HUMAN OTC DRUG LABEL
Date: 20241217

ACTIVE INGREDIENTS: BENZOCAINE 0.1 g/1 g
INACTIVE INGREDIENTS: SILICA; ASCORBIC ACID; EDETATE DISODIUM ANHYDROUS; ALOE BARBADENSIS LEAF JUICE; PEG-8 DIMETHICONE; RETINYL PALMITATE; PROPYLENE GLYCOL; PYRIDOXINE HCL; CHAMOMILE; DIAZOLIDINYL UREA; .ALPHA.-TOCOPHEROL ACETATE, D-; OCTYLDODECANOL; CAMPHOR, (-)-; ZEA MAYS (CORN) OIL; METHYLPARABEN; EUGENIA CARYOPHYLLUS (CLOVE) FLOWER OIL; MENTHA PIPERITA (PEPPERMINT) OIL; PEG-2 STEARATE; SODIUM PROPOXYHYDROXYPROPYL THIOSULFATE SILICA; WATER; CHOLECALCIFEROL; OLEA EUROPAEA (OLIVE) FRUIT; PROPYLPARABEN

Drug Facts

ACTIVE INGREDIENT

Benzocaine 10.0%

PURPOSE

Pain Relief

INDICATIONS AND USAGE

temporary relief of pain and itching due to

- chigger bites
- red bug bites
- ticks
- mosquito bites

WARNINGS

For external use only.

When using this product

- avoid contact with the eyes

Stop use and ask a doctor if

- condition worsens, or if symptoms persist for more than 7 days or clear up and occur again within a few days.

Keep out of reach of children. If swallowed, get medical help or contact a Poison Control Center right away.

INSTRUCTIONS FOR USE

Adults and children 2 years of age and older: Apply to affected area not more than 3 to 4 times daily. Children under 2 years of age: Ask a doctor.

INACTIVE INGREDIENT

Aloe Barbadensis Leaf Juice, Ascorbic Acid, Camphor, Chamomilla Recutita (Matricaria) Flower Extract, Cholecalciferol, Diazolidinyl Urea, Disodium EDTA, Eugenia Caryophyllus (Clove) Flower Oil, Fragrance,Mentha Piperita (Peppermint) Oil, Methylparaben, Octyldodecanol, Olea Europaea (Olive) Fruit Extract, PEG-2 Stearate, PEG-2 Stearate SE, PEG-8 Dimethicone, Propylene Glycol, Propylparaben, Pyridoxine HCl, Retinyl Palmitate, Sodium Propoxyhydroxypropyl Thiosulfate Silica, Tocopheryl Acetate, Water, Zea Mays (Corn) Oil

Distributed by:
Randob Labs, Ltd.
Box 440, Cornwall, NY 12518

DOSAGE AND ADMINISTRATION

Adults and children 2 years of age and older: Apply to affected area not more than 3 to 4 times daily. Children under 2 years of age: Ask a doctor.

Keep out of reach of children. If swallowed, get medical help or contact a Poison Control Center right away.

PACKAGE LABEL

THE ORIGINAL

Chiggerex®
2X Power!
with 10% Benzocaine
PAIN RELIEVING OINTMENT

FOR CHIGGER, TICK
AND ALL BUG BITES

FAST, SOOTHING RELIEF
With ALOE VERA
Plus CHAMOMILE

NET WT. 1.75 OZ. (50g)